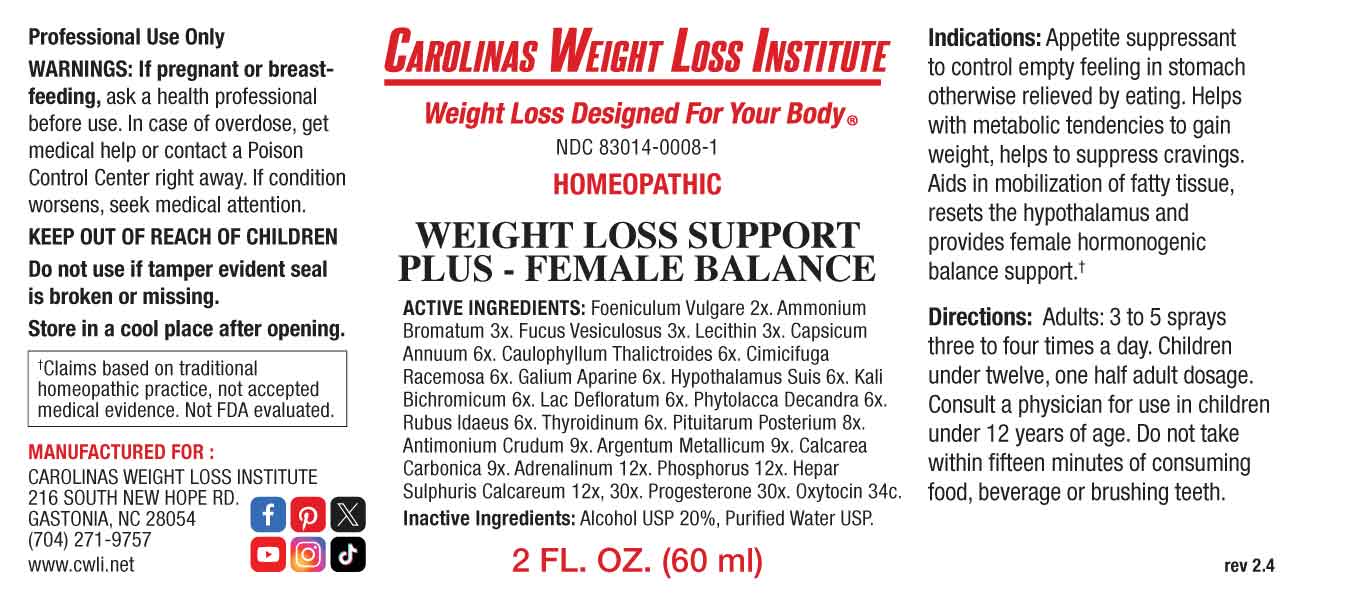 DRUG LABEL: Weight Loss Support Plus Female Balance
NDC: 83014-0008 | Form: SPRAY
Manufacturer: Carolinas Weight Loss Institute
Category: homeopathic | Type: HUMAN OTC DRUG LABEL
Date: 20240523

ACTIVE INGREDIENTS: FOENICULUM VULGARE FRUIT 2 [hp_X]/1 mL; AMMONIUM BROMIDE 3 [hp_X]/1 mL; FUCUS VESICULOSUS 3 [hp_X]/1 mL; EGG PHOSPHOLIPIDS 3 [hp_X]/1 mL; CAPSICUM 6 [hp_X]/1 mL; CAULOPHYLLUM THALICTROIDES ROOT 6 [hp_X]/1 mL; BLACK COHOSH 6 [hp_X]/1 mL; GALIUM APARINE WHOLE 6 [hp_X]/1 mL; SUS SCROFA HYPOTHALAMUS 6 [hp_X]/1 mL; POTASSIUM DICHROMATE 6 [hp_X]/1 mL; SKIM MILK 6 [hp_X]/1 mL; PHYTOLACCA AMERICANA ROOT 6 [hp_X]/1 mL; RUBUS IDAEUS LEAF 6 [hp_X]/1 mL; THYROID, BOVINE 6 [hp_X]/1 mL; BOS TAURUS PITUITARY GLAND, POSTERIOR 8 [hp_X]/1 mL; ANTIMONY TRISULFIDE 9 [hp_X]/1 mL; SILVER 9 [hp_X]/1 mL; OYSTER SHELL CALCIUM CARBONATE, CRUDE 9 [hp_X]/1 mL; EPINEPHRINE 12 [hp_X]/1 mL; PHOSPHORUS 12 [hp_X]/1 mL; CALCIUM SULFIDE 12 [hp_X]/1 mL; PROGESTERONE 30 [hp_X]/1 mL; OXYTOCIN 34 [hp_C]/1 mL
INACTIVE INGREDIENTS: WATER; ALCOHOL

DRUG FACTS:

ACTIVE INGREDIENTS:

Foeniculum Vulgare 2X, Ammonium Bromatum 3X, Fucus Vesiculosus 3X, Lecithin 3X, Capsicum Annuum 6X, Caulophyllum Thalictrines 6X, Cimicifuga Racemosa 6X, Galium Aparine 6X, Hypothalamus Suis 6X, Kali Bichromicum 6X, Lac Defloratum 6X, Phytolacca Decandra 6X, Rubus Idaeus 6X, Thyroidinum 6X, Pituitarum Posterium 8X, Antimonium Crudum 9X, Argentum Metallicum 9X, Calcarea Carbonica 9X, Adrenalinum 12X, Phosphorus 12X, Hepar Sulphuris Calcareum 12X, 30X, Progesterone 30X, Oxytocin 34C.

PURPOSE:

Appetite suppressant to control empty feeling in stomach otherwise relieved by eating. Helps with metabolic tendencies to gain weight, helps to suppress cravings. Aids in mobilization of fatty tissue, resets the hypothalamus and provides female hormonogenic balance support. †

†Claims based on traditional homeopathic practice, not accepted medical evidence. Not FDA evaluated.

WARNINGS:

Professional Use Only

If pregnant or breast-feeding, ask a health professional before use.

In case of overdose, get medical help or contact a Poison Control Center right away.

If condition worsens, seek medical attention.

KEEP OUT OF REACH OF CHILDREN

Do not use if tamper evident seal is broken or missing.

Store in a cool place after opening

KEEP OUT OF REACH OF CHILDREN:

In case of overdose, get medical help or contact a Poison Control Center right away.

DIRECTIONS:

Adults: 3 to 5 sprays three to four times a day. Children under twelve, one half adult dosage. Consult a physician for use in children under 12 years of age. Do not take within 15 minutes of consuming food, beverage or brushing teeth.

INDICATIONS:

Appetite suppressant to control empty feeling in stomach otherwise relieved by eating. Helps with metabolic tendencies to gain weight, helps to suppress cravings. Aids in mobilization of fatty tissue, resets the hypothalamus and provides female hormonogenic balance support. †

†Claims based on traditional homeopathic practice, not accepted medical evidence. Not FDA evaluated.

INACTIVE INGREDIENTS:

Alcohol USP 20%, Purified Water USP.

QUESTIONS:

MANUFACTURED FOR:

CAROLINAS WEIGHT LOSS INSTITUTE

216 SOUTH NEW HOPE RD.

GASTONIA, NC 28054

(704) 271-9757

www.cwli.net

PACKAGE LABEL DISPLAY:

CAROLINAS WEIGHT LOSS INSTITUTE

Weight Loss Designed For Your Body

NDC 83014-0008-1

HOMEOPATHIC

WEIGHT LOSS SUPPORT

PLUS - FEMALE BALANCE

2 FL. OZ. (60 ml)